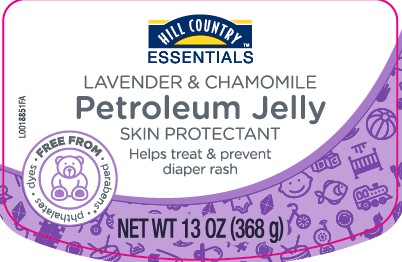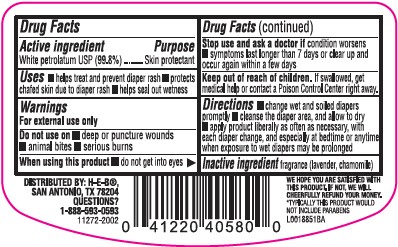 DRUG LABEL: Petroleum
NDC: 37808-015 | Form: JELLY
Manufacturer: H E B
Category: otc | Type: HUMAN OTC DRUG LABEL
Date: 20260224

ACTIVE INGREDIENTS: PETROLATUM 1 g/1 g

HEB Hill Country 566.001/566AA-AB
Petroleum Jelly Lavender and Chamomile

Active ingredient

White petrolatum USP (99.8%)

Purpose

Skin Protectant

Uses

- helps treat and prevent diaper rash
- protects chafed skin due to diaper rash
- helps seal out wetness

Warnings

For external use only

Do not use on

- deep or puncture wounds
- animal bites
- serious burns

When using this product

- do not get into eyes

Stop use and ask a doctor if

condition worsens

- symptoms last longer than 7 days or clear up and occur again within a few days

Keep out of reach of children.

If swallowed, get medical help or contact a Poison Control Center right away.

Directions

- change wet and soiled diapers promptly
- cleanse the diaper area, and allow to dry
- apply product liberally as often as necessary, with each diaper change, and especially at bedtime or anytime when exposure to wet diapers may be prolonged

Inactive ingredient

fragrance (lavender, chamomile)

ADVERSE REACTION

DISTRIBUTED BY: H-E-B®,

SAN ANTONIO, TX 78204

QUESTIONS? 1-888-593-0593

Claims

WE HOPE YOU ARE SATISFIED WITH THIS PRODUCT, IF NOT, WE WILL CHEERFULLY REFUND YOUR MONEY.

*TYPICALLY THIS PRODUCT WOULD NOT INCLUDE PARABENS

principal display panel

HILL COUNTRY™ ESSENTIALS

Lavender & Chamomile

Petroleum Jelly

Skin Protectant

Helps treat & prevent diaper rash

FREE FROM - parabens* • phthalates • dyes

NET WT 13 oz (368 g)